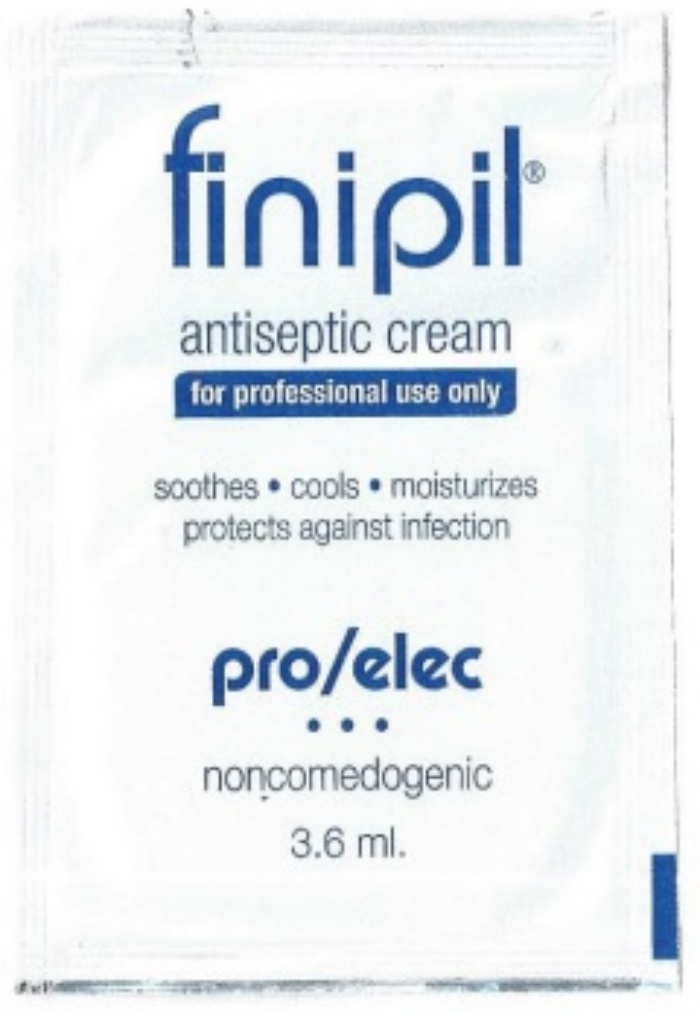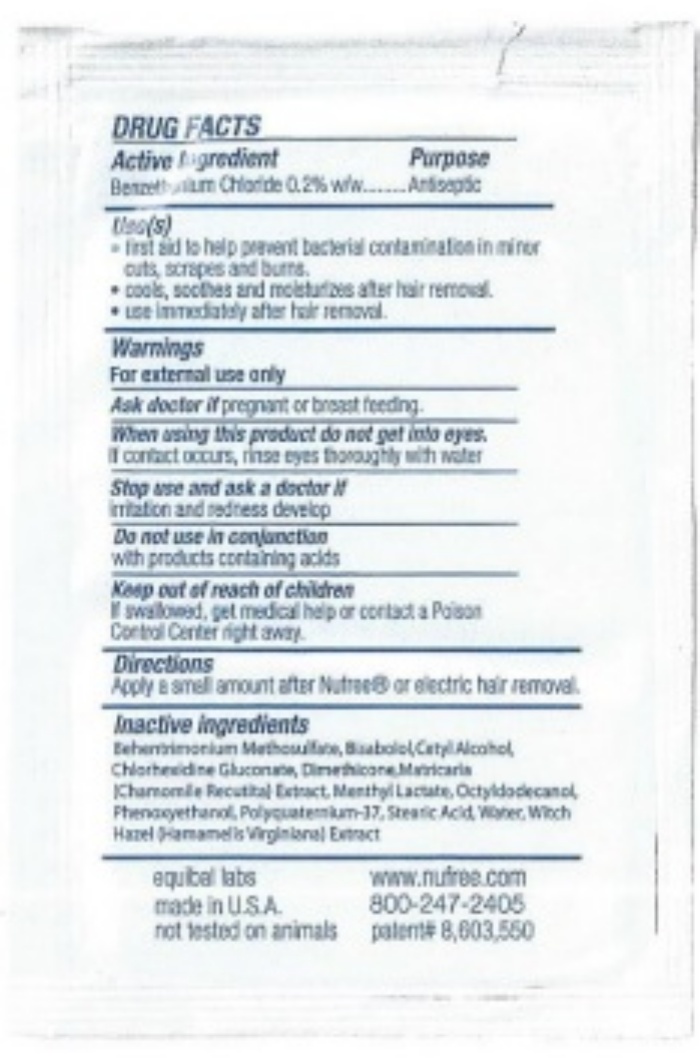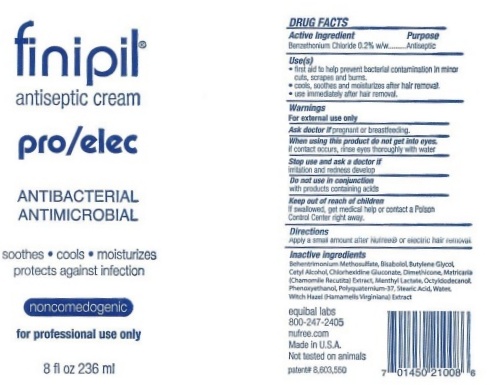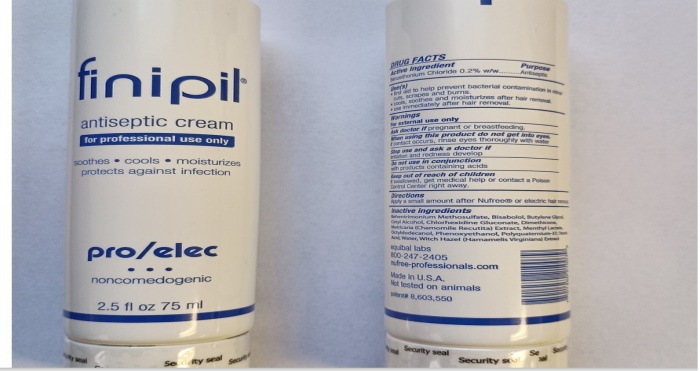 DRUG LABEL: finipil pro/elec

NDC: 53228-001 | Form: CREAM
Manufacturer: Equibal, Inc.
Category: otc | Type: HUMAN OTC DRUG LABEL
Date: 20251217

ACTIVE INGREDIENTS: BENZETHONIUM CHLORIDE 195 mg/100 mL
INACTIVE INGREDIENTS: BEHENTRIMONIUM METHOSULFATE; LEVOMENOL; BUTYLENE GLYCOL; CETYL ALCOHOL; CHLORHEXIDINE GLUCONATE; DIMETHICONE; MATRICARIA RECUTITA; MENTHYL LACTATE, (-)-; OCTYLDODECANOL; PHENOXYETHANOL; POLYQUATERNIUM-37 (25000 MPA.S); STEARIC ACID; WATER; HAMAMELIS VIRGINIANA TOP

FINIPIL PRO / ELEC

Active Ingredient

DRUG FACTS

Active Ingredient

Benzethonium Chloride 0.2% w/w

Purpose

Antiseptic

Keep out of reach of children.

If swallowed, get medical help or contact a Poison Control Center right away.

Use(s)

Uses(s)

- first aid to help prevent bacterial contamination in minor cuts, scrapes, and burns.
- cools, soothes, and moisturizes after hair removal.
- recommended for repeated use.

Warnings Do not use in conjunction

Warnings
For external use only
Do not use in conjunction
with products containing acids

Ask a doctor if

Ask a doctor ifpregnant or breast feeding,

Stop use and ask a doctor if

irritation and redness develop

Directions

Apply a small amount after Nufree® or electric hair removal

When using this product do not get into eyes.
If contact occurs, rinse eyes thoroughly with water.

Inactive ingredients

Behentrimonium Methosulfate, Bisabolol, Butylene Glycol, Cetyl Alcohol, Chlorhexidine Gluconate, Dimethicone, Matricaria (Chamomile Recutita) Extract, Menthyl Lactate, Octyldodecanol, Phenoxyethanol, Polyquarternium-37, Stearic Acid, Water, Witch Hazel (Hamamelis Virginiana) Extract

finipil pro/elec 3.6 ml

finipil®

antiseptic cream

for professional use only

soothes● cools● moisturizes

protects against infection

pro/elec

● ● ●

Noncomedogenic

3.6 ml.

DRUG FACTS

Active Ingredient Purpose

Benzethonium Chloride 0.2% w/w Antiseptic

Uses(s)

- first aid to help prevent bacterial contamination in minor cuts, scrapes, and burns.
- cools, soothes, and moisturizes after hair removal.
- recommended for repeated use.

Warnings

For external use only

Ask a doctor ifpregnant or breast feeding.

When using this product do not get into eyes.

if contact occurs, rinse eyes thoroughly with water.

Stop use and ask a doctor if

irritation and redness develop

Do not use in conjunction

with products containing acids.

Keep out of reach of children

if swallowed, get medical help or contact a Poison Control Center right away.

Directions

Apply a small amount of Nufree® or electric hair removal.

Inactive Ingredients

Bethecrimium methosulfate, Bisabolol, Cetyle Alcohol, Chlorhexidine Gluconate, Dimethicone, Matricaria (Chamomile Recutital) Extract, Menthyl Lactate, Octylodecanoil, Phenoxyethanol, Phenoxyethanol, Polyquaterniuim-37, Stearic Acid, Water, Witch Hazel (Hamamelis Virginiana) Extract

Equibal labs www.nufree.com

Made in U.S.A. 800-247-2405

not tested on animals patent# 8,603,550

finipil pro /elec 236 ml

finipil®

antiseptic cream

pro/elec

soothes● cools● moisturizes

protects against infection

Noncomedogenic

for professional use only

8 fl oz 236 ml

DRUG FACTS

Active Ingredient Purpose

Benzethonium Chloride 0.2% w/w Antiseptic

Uses(s)

- first aid to help prevent bacterial contamination in minor cuts, scrapes, and burns.
- cools, soothes, and moisturizes after hair removal.
- recommended for repeated use.

Warnings

For external use only

Ask a doctor ifpregnant or breast feeding.

When using this product do not get into eyes.

if contact occurs, rinse eyes thoroughly with water.

Stop use and ask a doctor if

irritation and redness develop

Do not use in conjunction

with products containing acids.

Keep out of reach of children

if swallowed, get medical help or contact a Poison Control Center right away.

Directions

Apply a small amount of Nufree® or electric hair removal.

Inactive Ingredients

Bethecrimium methosulfate, Bisabolol, Cetyle Alcohol, Chlorhexidine Gluconate, Dimethicone, Matricaria (Chamomile Recutital) Extract, Menthyl Lactate, Octylodecanoil, Phenoxyethanol, Phenoxyethanol, Polyquaterniuim-37, Stearic Acid, Water, Witch Hazel (Hamamelis Virginiana) Extract

equibal labs

800-247-2405

nufree.com

Made in U.S.A.

not tested on animals

patent# 8,603,550

finipil pro /elec 75 ml

finipil®

antiseptic cream

pro/elec

soothes ● cools ● moisturizes

protects against infection

Noncomedogenic

for professional use only

2.5 fl oz 75 ml

DRUG FACTS

Active Ingredient Purpose

Benzethonium Chloride 0.2% w/w Antiseptic

Uses(s)

first aid to help prevent bacterial contamination in minor cuts, scrapes, and burns.
cools, soothes, and moisturizes after hair removal.
recommended for repeated use.

Warnings

For external use only

Ask a doctor if pregnant or breast feeding.

When using this product do not get into eyes.

if contact occurs, rinse eyes thoroughly with water.

Stop use and ask a doctor if

irritation and redness develop

Do not use in conjunction

with products containing acids.

Keep out of reach of children

if swallowed, get medical help or contact a Poison Control Center right away.

Directions

Apply a small amount of Nufree® or electric hair removal.

Inactive Ingredients

Bethecrimium methosulfate, Bisabolol, Cetyle Alcohol, Chlorhexidine Gluconate, Dimethicone, Matricaria (Chamomile Recutital) Extract, Menthyl Lactate, Octylodecanoil, Phenoxyethanol, Phenoxyethanol, Polyquaterniuim-37, Stearic Acid, Water, Witch Hazel (Hamamelis Virginiana) Extract

equibal labs

800-247-2405

nufree.com

Made in U.S.A.

not tested on animals

patent# 8,603,550